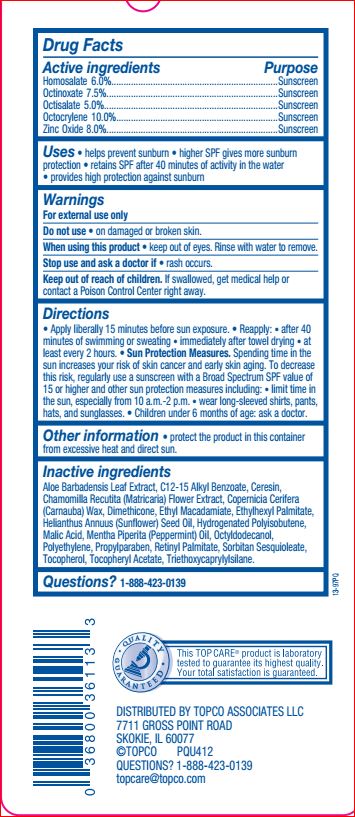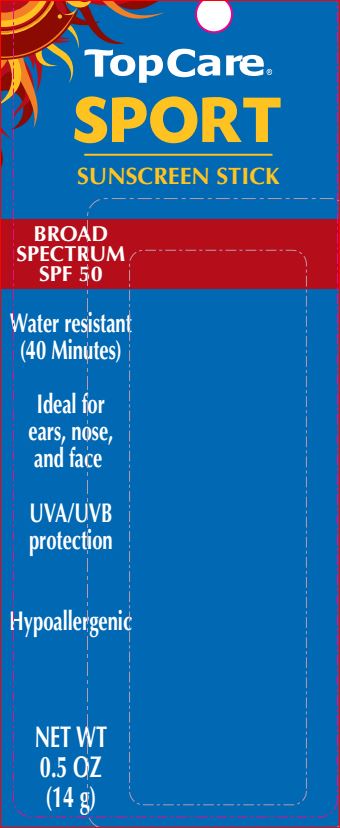 DRUG LABEL: Sport Sunscreen SPF 50
NDC: 36800-865 | Form: STICK
Manufacturer: TopCo
Category: otc | Type: HUMAN OTC DRUG LABEL
Date: 20180509

ACTIVE INGREDIENTS: Homosalate 6 g/100 g; Octinoxate 7.5 g/100 g; Octisalate 5 g/100 g; Octocrylene 10 g/100 g; Zinc Oxide 8 g/100 g
INACTIVE INGREDIENTS: ALOE VERA LEAF; ALKYL (C12-15) BENZOATE; Ceresin; CHAMOMILE; CARNAUBA WAX; Dimethicone; Ethyl Macadamiate; Ethylhexyl Palmitate; SUNFLOWER OIL; Malic Acid; PEPPERMINT OIL; Octyldodecanol; HIGH DENSITY POLYETHYLENE; Propylparaben; VITAMIN A PALMITATE; Sorbitan Sesquioleate; TOCOPHEROL; .ALPHA.-TOCOPHEROL ACETATE; Triethoxycaprylylsilane

Drug Facts

Active ingredients Purpose
Homosalate 6.0%....................................................................Sunscreen
Octinoxate 7.5%......................................................................Sunscreen
Octisalate 5.0%.......................................................................Sunscreen
Octocrylene 10.0%..................................................................Sunscreen
Zinc Oxide 8.0%......................................................................Sunscreen

INDICATIONS AND USAGE

Uses • helps prevent sunburn • higher SPF gives more sunburn
protection • retains SPF after 40 minutes of activity in the water
• provides high protection against sunburn

Warnings
For external use only
Do not use • on damaged or broken skin.
When using this product • keep out of eyes. Rinse with water to remove.
Stop use and ask a doctor if • rash occurs

Keep out of reach of children. If swallowed, get medical help or contact a Poison Control Center right away.

Directions
• Apply liberally 15 minutes before sun exposure. • Reapply: • after 40
minutes of swimming or sweating • immediately after towel drying • at
least every 2 hours. • Sun Protection Measures. Spending time in the
sun increases your risk of skin cancer and early skin aging. To decrease
this risk, regularly use a sunscreen with a Broad Spectrum SPF value of
15 or higher and other sun protection measures including: • limit time in
the sun, especially from 10 a.m.-2 p.m. • wear long-sleeved shirts, pants,
hats, and sunglasses. • Children under 6 months of age: ask a doctor

Other information • protect the product in this container from excessive heat and direct sun

Inactive ingredients
Aloe Barbadensis Leaf Extract, C12-15 Alkyl Benzoate, Ceresin,
Chamomilla Recutita (Matricaria) Flower Extract, Copernicia Cerifera
(Carnauba) Wax, Dimethicone, Ethyl Macadamiate, Ethylhexyl Palmitate,
Helianthus Annuus (Sunflower) Seed Oil, Hydrogenated Polyisobutene,
Malic Acid, Mentha Piperita (Peppermint) Oil, Octyldodecanol,
Polyethylene, Propylparaben, Retinyl Palmitate, Sorbitan Sesquioleate,
Tocopherol, Tocopheryl Acetate, Triethoxycaprylylsilane.